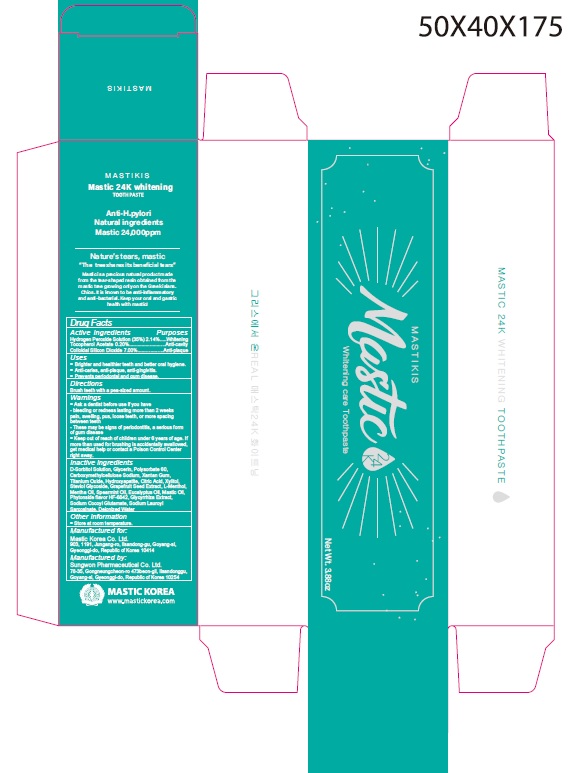 DRUG LABEL: Mastikis Mastic 24K Whitening
NDC: 79814-008 | Form: PASTE, DENTIFRICE
Manufacturer: Mastic Korea.Co.Ltd
Category: otc | Type: HUMAN OTC DRUG LABEL
Date: 20210128

ACTIVE INGREDIENTS: HYDROGEN PEROXIDE 2.14 g/100 g; .ALPHA.-TOCOPHEROL ACETATE 0.2 g/100 g; SILICON DIOXIDE 7 g/100 g
INACTIVE INGREDIENTS: SORBITOL; WATER; GLYCERIN; CARBOXYMETHYLCELLULOSE SODIUM, UNSPECIFIED; XANTHAN GUM; POLYSORBATE 60; TITANIUM DIOXIDE; XYLITOL; STEVIOSIDE; CITRUS PARADISI SEED; SODIUM LAUROYL SARCOSINATE; SPEARMINT OIL; TRIBASIC CALCIUM PHOSPHATE; LEVOMENTHOL; EUCALYPTUS OIL; LICORICE

79814-008_Mastikis Mastic 24K Whitening Toothpaste

ACTIVE INGREDIENT

Colloidal Silicon Dioxide 7%

Hydrogen Peroxide Solution 2.14%

Tocopherol Acetate 0.2%

INACTIVE INGREDIENT

D-Sorbitol Solution, Water, Glycerin, Mastic Oil, PCarboxymethylcellulose Sodium, Xantahan Gum, Polysorbate 60, Titanium Oxide, Citric Acid, Zylitol, Steviol Glycoside, Grapefruit Seed Extract, Sodium Lauroyl Sarcosinate, Sodium Cocoyl Glutamate, Mentha Oil, Spearmint oil, Tocopherol Acetate, Hydroxyapatite, L-Menthol, Eucalyptus Oil, Phytonside flavour, Glycyrrhiza Extract

Keep out of Reach of Children.

PURPOSE

Anti-gingivitis

Anti-plaque

WARNINGS

Ask a dentist before use if you have

- bleeding or redness lasting more than 2 weeks pain, swelling, pus, losse teeth, or more spacing between teeth

- These may be signs of periodontitis, a serious form of gum disease

INDICATIONS AND USAGE

- Brighter and healthier teeth and better oral hygiene

- Anti-caries, anti-plaque, anti--gingivitis

- Prevents periodontal and gum disease

DOSAGE AND ADMINISTRATION

Brush teeth with a pea-sized amount